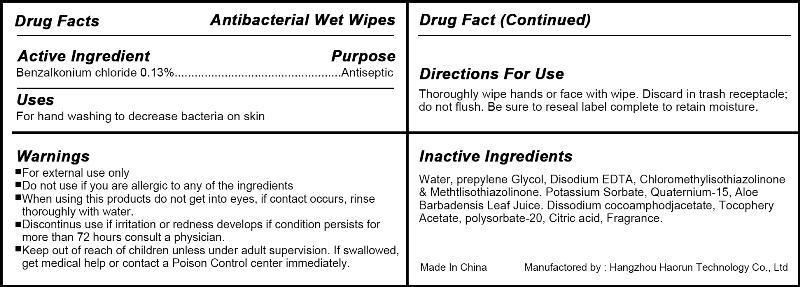 DRUG LABEL: antibacterial wet wipes
NDC: 57817-100 | Form: SWAB
Manufacturer: Hangzhou Haorun Technology CO.,LTD.
Category: otc | Type: HUMAN OTC DRUG LABEL
Date: 20130329

ACTIVE INGREDIENTS: Benzalkonium Chloride 0.13 g/100 g
INACTIVE INGREDIENTS: WATER; PROPYLENE GLYCOL; OCTHILINONE; .ALPHA.-TOCOPHEROL

Antibacterial Wet Wipes

Active Ingredient

Benzalkonium chloride 0.13%

Purpose

Antibacterial

Use

for hand washing to decrease bacteria on skin

WARNINGS

For External use only.
Do not use if you are allergic to any of the ingredients.
When using this product Do not get into eyes,if contact occurs ,rinse throughly with water.
Discontinue use if irritation or redness develops if condition persists for more than 72 hours consults a physician.

keep out of reach of children unless under adult supervision .if seallowed ,get medical help or contact a Poison Control Center immediately.

Directions

Thoroughly wipe hands or face with wipe,Discard in trash receptacle;do not flush.Be sure to reseal label complete to retain moisture

Inactive ingredients

WATER PROPYLENE GLYCOL OCTHILINONE .ALPHA.-TOCOPHEROL